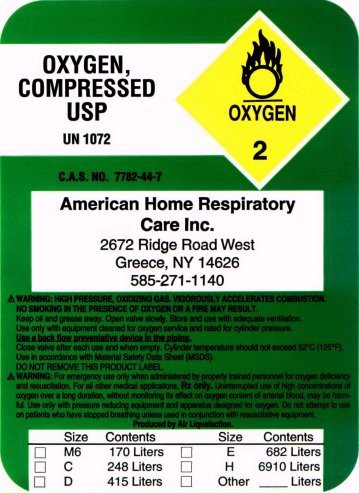 DRUG LABEL: Oxygen
NDC: 68515-001 | Form: GAS
Manufacturer: American Home Respiratory Care, Inc.
Category: prescription | Type: HUMAN PRESCRIPTION DRUG LABEL
Date: 20110103

ACTIVE INGREDIENTS: Oxygen 992 mL/1 L

PACKAGE LABEL

OXYGEN, COMPRESSED USP
UN 1072
OXYGEN 2
C.A.S. NO. 7782-44-7
American Home Respiratory Care Inc.
2672 Ridge Road West
Greece, NY 14626
585-271-1140
WARNING: HIGH PRESSURE, OXIDIZING GAS. VIGOROUSLY ACCELERATES COMBUSTION. NO SMOKING IN THE PRESENCE OF OXYGEN OR A FIRE MAY RESULT. Keep oil and grease away. Open valve slowly. Store and use with adequate ventilation. Use only with equipment cleaned for oxygen service and rated for cylinder pressure. Use a back flow preventative device in the piping. Close valve after each use and when empty. Cylinder temperature should not exceed 52oC (125oF). Use in accordance with Material Safety Data Sheet (MSDS).
DO NOT REMOVE THIS PRODUCT LABEL.
WARNING: For emergency use only when administered by properly trained personnel for oxygen deficiency and resuscitation. For all other medical applications, Rx only. Uninterrupted use of high concentrations of oxygen over a long duration, without monitoring its effect on oxygen content of arterial blood, may be harmful. Use only with pressure reducing equipment and apparatus designed for oxygen. Do not attempt to use on patients who have stopped breathing unless used in conjunction with resuscitative equipment.
Produced by Air Liquefaction.
Size Contents Size Contents
[ ] M6 170 Liters [ ] E 682 Liters
[ ] C 248 Liters [ ] H 6910 Liters
[ ] D 415 Liters [ ] Other ____ Liters